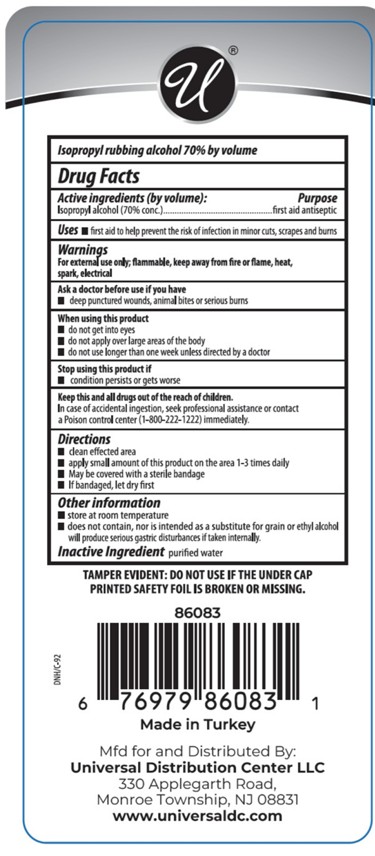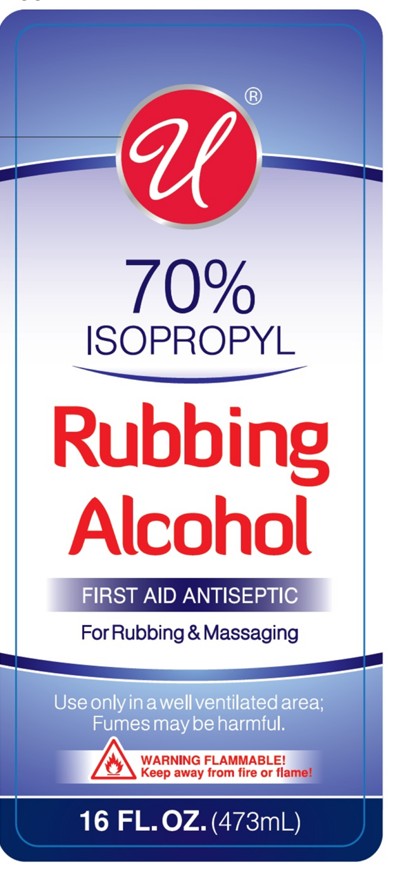 DRUG LABEL: UNIVERSAL ISOPROPYL RUBBING ALCOHOL 70% - isopropyl alcohol liquid
NDC: 76567-4301 | Form: LIQUID
Manufacturer: TSM BRANDS LLC
Category: otc | Type: HUMAN OTC DRUG LABEL
Date: 20250630

ACTIVE INGREDIENTS: ISOPROPYL ALCOHOL 331 mL/473 mL
INACTIVE INGREDIENTS: WATER 142 mL/473 mL

UNIVERSAL ISOPROPYL RUBBING ALCOHOL %70

Active Ingredients

Isopropyl Alcohol

Ask a doctor before use if you have

Deep punctured wounds, animal bites or serious burns

Stop using this product if

conditions persists or gets worse

Keep this and all drugs out of reach of the children

In case of accidental ingestion, seek professional assistance or contact a Poison control control center (1-800-222-1222) immediately

Purpose

First aid antiseptic

Stop using this product if

condition persist or gets worse

When using this product

Do not get into eyes

Do not apply over large areas of the body

Do not use longer than one week unless directed by a doctor

Warnngs

For external use only, flammable, keep away from fire or flammable, heat, spark, electrical

Directions

clean effected area

apply small amount of this product on the area 1-3 times daily

May be covered with a sterile bandage

If bandaged, let dry firs

Inactive Ingredient

purified water

Uses

first aid to help prevent the risk of infection in minor cuts, scrapes and burns